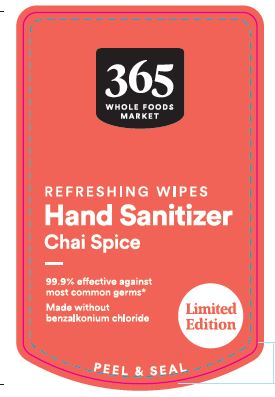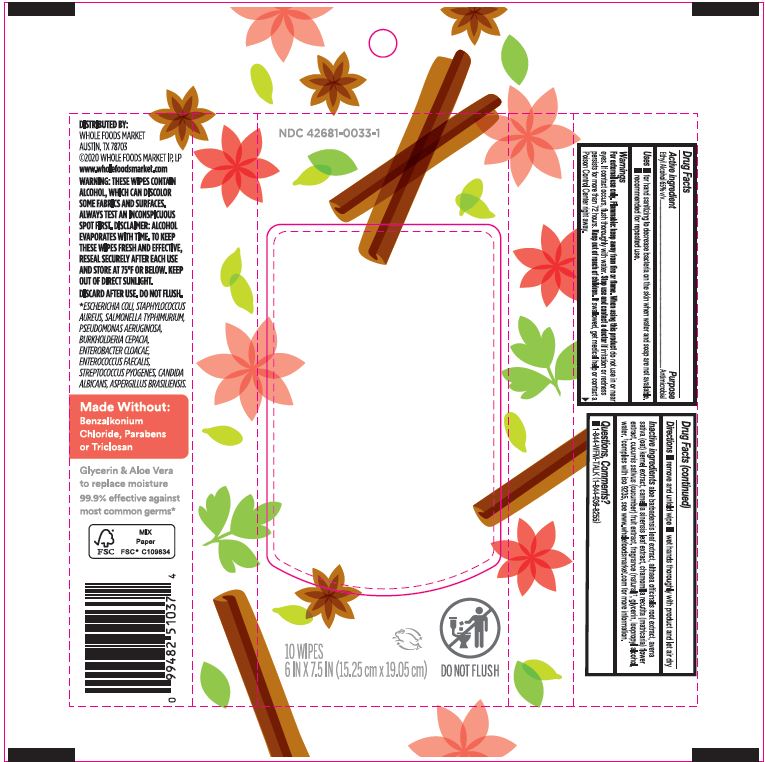 DRUG LABEL: 365 Chai Spice Hand Sanitizer Wipes
NDC: 42681-0033 | Form: CLOTH
Manufacturer: Whole Foods Market, Inc.
Category: otc | Type: HUMAN OTC DRUG LABEL
Date: 20251009

ACTIVE INGREDIENTS: ALCOHOL 65 mL/100 mL
INACTIVE INGREDIENTS: OAT KERNEL OIL; WATER; ALOE VERA LEAF; ALTHAEA OFFICINALIS ROOT; GLYCERIN; TEA LEAF; MATRICARIA CHAMOMILLA FLOWERING TOP; CUCUMIS SATIVUS WHOLE; ISOPROPYL ALCOHOL

365 Chai Spice Hand Sanitizer Wipes 10ct

Active Ingredient

Ethyl Alcohol 65% v/v

Purpose

Antimicrobial

Uses

• for hand sanitizing to decrease bacteria on skin when water and soap are not avaliable

• recommended for repeated use

Warnings

For external use only.

Flammable keep away from fire or flame.

When using this product do not use in or near eyes, if contact occurs, flush thoroughly with water.

Stop use and contact a doctor if irritation or redness persists for more than 72 hours.

Keep out of reach of children. If swallowed, get medical help or contact a Poison Control Center right away

Directions

• remove and unfold wipe

•wet hands thoroughly with product and let air dry

Inactive ingredients

Aloe Barbadensis Leaf Extract
Althaea Officinalis Root Extract
Avena Sativa (Oat) Kernel Extract
Camellia Sinensis Leaf Extract
Chamomilla Recutita (Matricaria) Flower Extract
Cucumis Sativus (Cucumber) Fruit Extract
Glycerin

[complies with iso 9235, see www.wholefoodsmarket.com form more information.] Fragrance(natural)

Isopropyl alcohol

Water.

Questions, Comments?

1-844-WFM-TALK(1-844-936-8255)

Label

NDC 42681-0033-1

365 WHOLE FOODS MARKET

REFRESHING WIPES

Hand Sanitizer

Chai Spice

99.9% effective against most common germs*

Made without benzalkonium chloride

Limited Edition

PEEL & SEAL

10 WIPES

6IN x 7.5IN (15.25cm x 19.05cm)

DO NOT FLUSH

DISTRIBUTED BY: WHOLE FOODS MARKET

AUSTIN, TX 78703

2020 WHOLE FOODS MARKET IP, LP

www.wholefoodsmarket.com

WARNING: THESE WIPES CONTAIN ALCOHOL, WHICH CAN DISCOLOR SOME FABRICS AND SURFACES. ALWAYS TEST AN INCONSPICUOUS SPOT FIRST. DISCLAIMER: ALCOHOL EVAPORATES WITH TIME. TO KEEP THESE WIPES FRESH AND EFFECTIVE RESEAL SECURELY AFTER EACH USE AND STORE AT 75F OR BELOW. KEEP OUT OF DIRECT SUNLIGHT.

DISCARD AFTER USE. DO NOT FLUSH.

*ESCHERICHIA COLI, STAPHYLOCOCCUS AUREUS, SALMONELLA TYPHIMURIUM, PSEUDOMONAS AERUGINOSA, BURKHOLDERIA CEPACIA, ENTEROBACTER CLOACAE, ENTEROCOCCUS FAECALIS, STREPTOCOCCUS PYOGENES, CANDIDA ALBICANS, ASPERGILLUS BRASILIENSIS.

Made Without:

Benzalkonium Chloride, Parabens or Triclosan

Glycerin & Aloe Vera to replace moisture

99.9% effective against most common germs*

FSC MIX Paper

FSC C109834

UPC 099482510374